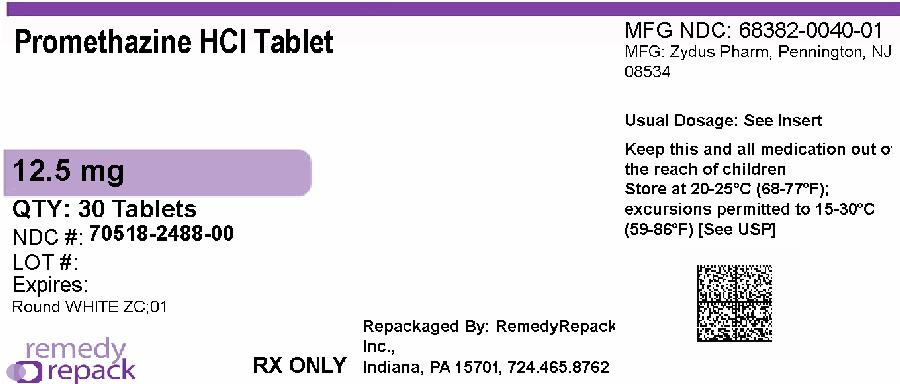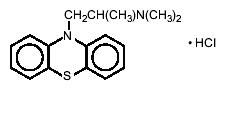 DRUG LABEL: Promethazine Hydrochloride
NDC: 70518-2488 | Form: TABLET
Manufacturer: REMEDYREPACK INC.
Category: prescription | Type: HUMAN PRESCRIPTION DRUG LABEL
Date: 20260206

ACTIVE INGREDIENTS: PROMETHAZINE HYDROCHLORIDE 12.5 mg/1 1
INACTIVE INGREDIENTS: HYDROXYPROPYL CELLULOSE, UNSPECIFIED; HYDROXYPROPYL CELLULOSE, LOW SUBSTITUTED; LACTOSE MONOHYDRATE; MAGNESIUM STEARATE

Promethazine Hydrochloride Tablets USP

DESCRIPTION

Each tablet of promethazine hydrochloride contains 12.5 mg, 25 mg, or 50 mg promethazine hydrochloride. The inactive ingredients present are hydroxypropyl cellulose, lactose monohydrate, low-substituted hydroxypropyl cellulose and magnesium stearate.

Promethazine hydrochloride is a racemic compound; the molecular formula is C17H20N2S HCl and its molecular weight is 320.88.

Promethazine hydrochloride, a phenothiazine derivative, is designated chemically as 10 H-Phenothiazine-10-ethanamine, N, N,α-trimethyl-, monohydrochloride, (±)- with the following structural formula.

Promethazine hydrochloride occurs as a white to faint yellow, practically odorless, crystalline powder which slowly oxidizes and turns blue on prolonged exposure to air. It is freely soluble in water, in hot dehydrated alcohol, and in chloroform; practically insoluble in ether, in acetone and in ethyl acetate.

CLINICAL PHARMACOLOGY

Promethazine is a phenothiazine derivative which differs structurally from the antipsychotic phenothiazines by the presence of a branched side chain and no ring substitution. It is thought that this configuration is responsible for its relative lack (1/10 that of chlorpromazine) of dopamine antagonist properties.

Promethazine is an H1receptor blocking agent. In addition to its antihistaminic action, it provides clinically useful sedative and antiemetic effects.

Promethazine is well absorbed from the gastrointestinal tract. Clinical effects are apparent within 20 minutes after oral administration and generally last four to six hours, although they may persist as long as 12 hours. Promethazine is metabolized by the liver to a variety of compounds; the sulfoxides of promethazine and N-demethylpromethazine are the predominant metabolites appearing in the urine.

INDICATIONS AND USAGE

Promethazine Hydrochloride, is useful orally for.

Perennial and seasonal allergic rhinitis.

Vasomotor rhinitis.

Allergic conjunctivitis due to inhalant allergens and foods.

Mild, uncomplicated allergic skin manifestations of urticaria and angioedema.

Amelioration of allergic reactions to blood or plasma.

Dermographism.

Anaphylactic reactions, as adjunctive therapy to epinephrine and other standard measures, after the acute manifestations have been controlled.

Preoperative, postoperative, or obstetric sedation.

Prevention and control of nausea and vomiting associated with certain types of anesthesia and surgery.

Therapy adjunctive to meperidine or other analgesics for control of post-operative pain.

Sedation in both children and adults, as well as relief of apprehension and production of light sleep from which the patient can be easily aroused.

Active and prophylactic treatment of motion sickness.

Antiemetic therapy in postoperative patients.

CONTRAINDICATIONS

Promethazine hydrochloride tablets, USP are contraindicated for use in pediatric patients less than two years of age.

Promethazine hydrochloride tablets, USP are contraindicated in comatose states, and in individuals known to be hypersensitive or to have had an idiosyncratic reaction to promethazine or to other phenothiazines.

Antihistamines are contraindicated for use in the treatment of lower respiratory tract symptoms including asthma.

WARNINGS

BOXED WARNING

PROMETHAZINE HYDROCHLORIDE TABLETS, USP SHOULD NOT BE USED IN PEDIATRIC PATIENTS LESS THAN 2 YEARS OF AGE BECAUSE OF THE POTENTIAL FOR FATAL RESPIRATORY DEPRESSION.

POSTMARKETING CASES OF RESPIRATORY DEPRESSION, INCLUDING FATALITIES, HAVE BEEN REPORTED WITH USE OF PROMETHAZINE HYDROCHLORIDE TABLETS, USP IN PEDIATRIC PATIENTS LESS THAN 2 YEARS OF AGE. A WIDE RANGE OF WEIGHT-BASED DOSES OF PROMETHAZINE HYDROCHLORIDE TABLETS, USP HAVE RESULTED IN RESPIRATORY DEPRESSION IN THESE PATIENTS.

CAUTION SHOULD BE EXERCISED WHEN ADMINISTERING PROMETHAZINE HYDROCHLORIDE TABLETS, USP TO PEDIATRIC PATIENTS 2 YEARS OF AGE AND OLDER. IT IS RECOMMENDED THAT THE LOWEST EFFECTIVE DOSE OF PROMETHAZINE HYDROCHLORIDE BE USED IN PEDIATRIC PATIENTS 2 YEARS OF AGE AND OLDER AND CONCOMITANT ADMINISTRATION OF OTHER DRUGS WITH RESPIRATORY DEPRESSANT EFFECTS BE AVOIDED.

CNS Depression

Promethazine hydrochloride tablets, USP may impair the mental and/or physical abilities required for the performance of potentially hazardous tasks, such as driving a vehicle or operating machinery. The impairment may be amplified by concomitant use of other central-nervous-system depressants such as alcohol, sedatives/hypnotics (including barbiturates), narcotics, narcotic analgesics, general anesthetics, tricyclic antidepressants, and tranquilizers; therefore such agents should either be eliminated or given in reduced dosage in the presence of promethazine hydrochloride (see PRECAUTIONS Information for Patientsand Drug Interactions)

Respiratory Depression

Promethazine hydrochloride tablets, USP may lead to potentially fatal respiratory depression.

Use of promethazine hydrochloride tablets, USP in patients with compromised respiratory function (e.g., COPD, sleep apnea) should be avoided.

Lower Seizure Threshold

Promethazine hydrochloride tablets, USP may lower seizure threshold. It should be used with caution in persons with seizure disorders or in persons who are using concomitant medications, such as narcotics or local anesthetics, which may also affect seizure threshold.

Bone-Marrow Depression

Promethazine hydrochloride tablets, USP should be used with caution in patients with bone-marrow depression. Leukopenia and agranulocytosis have been reported, usually when promethazine hydrochloride has been used in association with other known marrow-toxic agents.

Neuroleptic Malignant Syndrome

A potentially fatal symptom complex sometimes referred to as Neuroleptic Malignant Syndrome (NMS) has been reported in association with promethazine hydrochloride alone or in combination with antipsychotic drugs. Clinical manifestations of NMS are hyperpyrexia, muscle rigidity, altered mental status and evidence of autonomic instability (irregular pulse or blood pressure, tachycardia, diaphoresis and cardiac dysrhythmias).

The diagnostic evaluation of patients with this syndrome is complicated. In arriving at a diagnosis, it is important to identify cases where the clinical presentation includes both serious medical illness (e.g., pneumonia, systemic infection, etc.) and untreated or inadequately treated extrapyramidal signs and symptoms (EPS). Other important considerations in the differential diagnosis include central anticholinergic toxicity, heat stroke, drug fever and primary central nervous system (CNS) pathology.

The management of NMS should include 1) immediate discontinuation of promethazine hydrochloride, antipsychotic drugs, if any, and other drugs not essential to concurrent therapy, 2) intensive symptomatic treatment and medical monitoring, and 3) treatment of any concomitant serious medical problems for which specific treatments are available. There is no general agreement about specific pharmacological treatment regimens for uncomplicated NMS.

Since recurrences of NMS have been reported with phenothiazines, the reintroduction of promethazine hydrochloride should be carefully considered.

Use in Pediatric Patients

PROMETHAZINE HYDROCHLORIDE TABLETS, USP ARE CONTRAINDICATED FOR USE IN PEDIATRIC PATIENTS LESS THAN TWO YEARS OF AGE.

CAUTION SHOULD BE EXERCISED WHEN ADMINISTERING PROMETHAZINE HYDROCHLORIDE TABLETS, USP TO PEDIATRIC PATIENTS 2 YEARS OF AGE AND OLDER BECAUSE OF THE POTENTIAL FOR FATAL RESPIRATORY DEPRESSION. RESPIRATORY DEPRESSION AND APNEA, SOMETIMES ASSOCIATED WITH DEATH, ARE STRONGLY ASSOCIATED WITH PROMETHAZINE PRODUCTS AND ARE NOT DIRECTLY RELATED TO INDIVIDUALIZED WEIGHT-BASED DOSING, WHICH MIGHT OTHERWISE PERMIT SAFE ADMINISTRATION. CONCOMITANT ADMINISTRATION OF PROMETHAZINE PRODUCTS WITH OTHER RESPIRATORY DEPRESSANTS HAS AN ASSOCIATION WITH RESPIRATORY DESPRESSION, AND SOMETIMES DEATH, IN PEDIATRIC PATIENTS.

ANTIEMETICS ARE NOT RECOMMENDED FOR TREATMENT OF UNCOMPLICATED VOMITING IN PEDIATRIC PATIENTS, AND THEIR USE SHOULD BE LIMITED TO PROLONGED VOMITING OF KNOWN ETIOLOGY. THE EXTRAPYRAMIDAL SYMPTOMS WHICH CAN OCCUR SECONDARY TO PROMETHAZINE HYDROCHLORIDE TABLETS, USP ADMINISTRATION MAY BE CONFUSED WITH THE CNS SIGNS OF UNDIAGNOSED PRIMARY DISEASE, e.g., ENCEPHALOPATHY OR REYE'S SYNDROME. THE USE OF PROMETHAZINE HYDROCHLORIDE TABLETS, USP SHOULD BE AVOIDED IN PEDIATRIC PATIENTS WHOSE SIGNS AND SYMPTOMS MAY SUGGEST REYE'S SYNDROME OR OTHER HEPATIC DISEASES.

Excessively large dosages of antihistamines, including promethazine hydrochloride tablets, USP in pediatric patients may cause sudden death (see OVERDOSAGE).Hallucinations and convulsions have occurred with therapeutic doses and overdoses of promethazine hydrochloride in pediatric patients. In pediatric patients who are acutely ill associated with dehydration, there is an increased susceptibility to dystonias with the use of promethazine hydrochloride.

Other Considerations

Administration of promethazine hydrochloride has been associated with reported cholestatic jaundice.

PRECAUTIONS

General

Drugs having anticholinergic properties should be used with caution in patients with narrow-angle glaucoma, prostatic hypertrophy, stenosing peptic ulcer, pyloroduodenal obstruction, and bladder-neck obstruction.

Promethazine hydrochloride tablets, USP should be used cautiously in persons with cardiovascular disease or with impairment of liver function.

Information for Patients

Promethazine hydrochloride tablets, USP may cause marked drowsiness or impair the mental and/or physical abilities required for the performance of potentially hazardous tasks, such as driving a vehicle or operating machinery. The use of alcohol or other central-nervous-system depressants such as sedatives/hypnotics (including barbiturates), narcotics, narcotic analgesics, general anesthetics, tricyclic antidepressants, and tranquilizers, may enhance impairment (see WARNINGS-CNS Depressionand PRECAUTIONS-Drug Interactions). Pediatric patients should be supervised to avoid potential harm in bike riding or in other hazardous activities.

Patients should be advised to report any involuntary muscle movements.

Avoid prolonged exposure to the sun.

Repackaged By / Distributed By: RemedyRepack Inc.

625 Kolter Drive, Indiana, PA 15701

(724) 465-8762

Drug Interactions

CNS Depressants- Promethazine hydrochloride tablets, USP may increase, prolong, or intensify the sedative action of other central-nervous-system depressants, such as alcohol, sedatives/hypnotics (including barbiturates), narcotics, narcotic analgesics, general anesthetics, tricyclic antidepressants, and tranquilizers; therefore, such agents should be avoided or administered in reduced dosage to patients receiving promethazine hydrochloride. When given concomitantly with promethazine hydrochloride tablets, USP the dose of barbiturates should be reduced by at least one-half, and the dose of narcotics should be reduced by one-quarter to one-half. Dosage must be individualized. Excessive amounts of promethazine hydrochloride relative to a narcotic may lead to restlessness and motor hyperactivity in the patient with pain; these symptoms usually disappear with adequate control of the pain.

Epinephrine- Because of the potential for promethazine hydrochloride to reverse epinephrine's vasopressor effect, epinephrine should NOT be used to treat hypotension associated with promethazine hydrochloride tablets, USP overdose.

Anticholinergics- Concomitant use of other agents with anticholinergic properties should be undertaken with caution.

Monoamine Oxidase Inhibitors (MAOI)- Drug interactions, including an increased incidence of extrapyramidal effects, have been reported when some MAOI and phenothiazines are used concomitantly. This possibility should be considered with promethazine hydrochloride tablets, USP.

Drug/Laboratory Test Interactions

The following laboratory tests may be affected in patients who are receiving therapy with promethazine hydrochloride:

Pregnancy Tests

Diagnostic pregnancy tests based on immunological reactions between HCG and anti-HCG may result in false-negative or false-positive interpretations.

Glucose Tolerance Test

An increase in blood glucose has been reported in patients receiving promethazine hydrochloride.

Carcinogenesis, Mutagenesis, Impairment of Fertility

Long-term animal studies have not been performed to assess the carcinogenic potential of promethazine, nor are there other animal or human data concerning carcinogenicity, mutagenicity, or impairment of fertility with this drug. Promethazine was nonmutagenic in the Salmonellatest system of Ames.

Pregnancy

Teratogenic Effects - Pregnancy Category C

Teratogenic effects have not been demonstrated in rat-feeding studies at doses of 6.25 and 12.5 mg/kg of promethazine hydrochloride. These doses are from approximately 2.1 to 4.2 times the maximum recommended total daily dose of promethazine for a 50-kg subject, depending upon the indication for which the drug is prescribed. Daily doses of 25 mg/kg intraperitoneally have been found to produce fetal mortality in rats.

Specific studies to test the action of the drug on parturition, lactation, and development of the animal neonate were not done, but a general preliminary study in rats indicated no effect on these parameters. Although antihistamines have been found to produce fetal mortality in rodents, the pharmacological effects of histamine in the rodent do not parallel those in man. There are no adequate and well-controlled studies of promethazine hydrochloride tablets, USP in pregnant women.

Promethazine hydrochloride tablets, USP should be used during pregnancy only if the potential benefit justifies the potential risk to the fetus.

Nonteratogenic Effects-

Promethazine hydrochloride tablets, USP administered to a pregnant woman within two weeks of delivery may inhibit platelet aggregation in the newborn.

Labor and Delivery

Promethazine hydrochloride may be used alone or as an adjunct to narcotic analgesics during labor (DOSAGE AND ADMINISTRATION). Limited data suggest that use of promethazine hydrochloride during labor and delivery does not have an appreciable effect on the duration of labor or delivery and does not increase the risk of need for intervention in the newborn. The effect on later growth and development of the newborn is unknown (see also Nonteratogenic Effects).

Nursing Mothers

It is not known whether promethazine hydrochloride is excreted in human milk. Because many drugs are excreted in human milk and because of the potential for serious adverse reactions in nursing infants from promethazine hydrochloride tablets, USP a decision should be made whether to discontinue nursing or to discontinue the drug, taking into account the importance of the drug to the mother.

Pediatric Use

PROMETHAZINE HYDROCHLORIDE TABLETS, USP ARE CONTRAINDICATED FOR USE IN PEDIATRIC PATIENTS LESS THAN TWO YEARS OF AGE(see WARNINGS-BLACK BOX Warningand Use in Pediatric Patients).

Promethazine hydrochloride tablets, USP should be used with caution in pediatric patients 2 years of age and older (see WARNINGS-Use in Pediatric Patients).

Geriatric Use

Clinical studies of promethazine hydrochloride formulations did not include sufficient numbers of subjects aged 65 and over to determine whether they respond differently from younger subjects. Other reported clinical experience has not identified differences in responses between the elderly and younger patients. In general, dose selection for an elderly patient should be cautious, usually starting at the low end of the dosing range, reflecting the greater frequency of decreased hepatic, renal or cardiac function, and of concomitant disease or other drug therapy.

Sedating drugs may cause confusion and over-sedation in the elderly; elderly patients generally should be started on low doses of promethazine hydrochloride tablets, USP and observed closely.

ADVERSE REACTIONS

Central Nervous System

Drowsiness is the most prominent CNS effect of this drug. Sedation, somnolence, blurred vision, dizziness; confusion, disorientation, and extrapyramidal symptoms such as oculogyric crisis, torticollis, and tongue protrusion; lassitude, tinnitus, incoordination, fatigue, euphoria, nervousness, diplopia, insomnia, tremors, convulsive seizures, excitation, catatonic-like states, hysteria. Hallucinations have also been reported.

Cardiovascular-Increased or decreased blood pressure, tachycardia, bradycardia, faintness.

Dermatologic- Dermatitis, photosensitivity, urticaria.

Hematologic-Leukopenia, thrombocytopenia, thrombocytopenic purpura, agranulocytosis.

Gastrointestinal-Dry mouth, nausea, vomiting, jaundice.

Respiratory-Asthma, nasal stuffiness, respiratory depression (potentially fatal) and apnea (potentially fatal) (see WARNINGS-Respiratory Depression).

Other-Angioneurotic edema. Neuroleptic malignant syndrome (potentially fatal) has also been reported (see WARNINGS-Neuroleptic Malignant Syndrome).

Paradoxical Reactions

Hyperexcitability and abnormal movements have been reported in patients following a single administration of promethazine hydrochloride. Consideration should be given to the discontinuation of promethazine hydrochloride and to the use of other drugs if these reactions occur. Respiratory depression, nightmares, delirium, and agitated behavior have also been reported in some of these patients.

OVERDOSAGE

Signs and symptoms of overdosage with promethazine hydrochloride range from mild depression of the central nervous system and cardiovascular system to profound hypotension, respiratory depression, unconsciousness, and sudden death. Other reported reactions include hyperreflexia, hypertonia, ataxia, athetosis, and extensor-plantar reflexes (Babinski reflex).

Stimulation may be evident, especially in children and geriatric patients. Convulsions may rarely occur. A paradoxical-type reaction has been reported in children receiving single doses of 75 mg to 125 mg orally, characterized by hyperexcitability and nightmares.

Atropine-like signs and symptoms-dry mouth, fixed, dilated pupils, flushing, as well as gastrointestinal symptoms-may occur.

Treatment

Treatment of overdosage is essentially symptomatic and supportive. Only in cases of extreme overdosage or individual sensitivity do vital signs, including respiration, pulse, blood pressure, temperature, and EKG, need to be monitored. Activated charcoal orally or by lavage may be given, or sodium or magnesium sulfate orally as a cathartic. Attention should be given to the reestablishment of adequate respiratory exchange through provision of a patent airway and institution of assisted or controlled ventilation. Diazepam may be used to control convulsions. Acidosis and electrolyte losses should be corrected. Note that any depressant effects of promethazine hydrochloride are not reversed by naloxone. Avoid analeptics which may cause convulsions.

The treatment of choice for resulting hypotension is administration of intravenous fluids, accompanied by repositioning if indicated. In the event that vasopressors are considered for the management of severe hypotension which does not respond to intravenous fluids and repositioning, the administration of norepinephrine or phenylephrine should be considered. EPINEPHRINE SHOULD NOT BE USED, since its use in patients with partial adrenergic blockade may further lower the blood pressure. Extrapyramidal reactions may be treated with anticholinergic antiparkinsonian agents, diphenhydramine, or barbiturates. Oxygen may also be administered.

Limited experience with dialysis indicates that it is not helpful.

DOSAGE AND ADMINISTRATION

Promethazine hydrochloride tablets, USP are contraindicated for children under 2 years of age(see WARNINGS-Black Box Warningand Use in Pediatric Patients).

Allergy

The average oral dose is 25 mg taken before retiring; however, 12.5 mg may be taken before meals and on retiring, if necessary. Single 25-mg doses at bedtime or 6.25 to 12.5 mg taken three times daily will usually suffice. After initiation of treatment in children or adults, dosage should be adjusted to the smallest amount adequate to relieve symptoms. The administration of promethazine hydrochloride in 25-mg doses will control minor transfusion reactions of an allergic nature.

Motion Sickness

The average adult dose is 25 mg taken twice daily. The initial dose should be taken one-half to one hour before anticipated travel and be repeated 8 to 12 hours later, if necessary. On succeeding days of travel, it is recommended that 25 mg be given on arising and again before the evening meal. For children, promethazine hydrochloride tablets, USP, 12.5 to 25 mg, twice daily, may be administered.

Nausea and Vomiting

Antiemetics should not be used in vomiting of unknown etiology in children and adolescents (see WARNINGS-Use in Pediatric Patients).

The average effective dose of promethazine hydrochloride for the active therapy of nausea and vomiting in children or adults is 25 mg. When oral medication cannot be tolerated, the dose should be given parenterally (cf. Promethazine hydrochloride Injection). 12.5- to 25-mg doses may be repeated, as necessary, at 4- to 6-hour intervals.

For nausea and vomiting in children, the usual dose is 0.5 mg per pound of body weight, and the dose should be adjusted to the age and weight of the patient and the severity of the condition being treated.

For prophylaxis of nausea and vomiting, as during surgery and the postoperative period, the average dose is 25 mg repeated at 4- to 6-hour intervals, as necessary.

Sedation

This product relieves apprehension and induces a quiet sleep from which the patient can be easily aroused. Administration of 12.5 to 25 mg promethazine hydrochloride by the oral route or by rectal suppository at bedtime will provide sedation in children. Adults usually require 25 to 50 mg for nighttime, presurgical, or obstetrical sedation.

Pre- and Postoperative Use

Promethazine hydrochloride in 12.5- to 25-mg doses for children and 50-mg doses for adults the night before surgery relieves apprehension and produces a quiet sleep.

For preoperative medication, children require doses of 0.5 mg per pound of body weight in combination with an appropriately reduced dose of narcotic or barbiturate and the appropriate dose of an atropine-like drug. Usual adult dosage is 50 mg promethazine hydrochloride with an appropriately reduced dose of narcotic or barbiturate and the required amount of a belladonna alkaloid.

Postoperative sedation and adjunctive use with analgesics may be obtained by the administration of 12.5 to 25 mg in children and 25- to 50-mg doses in adults.

Promethazine hydrochloride tablets, USP are contraindicated for children under 2 years of age.

HOW SUPPLIED

Promethazine hydrochloride tablets USP, 12.5 mg are white to off-white, round shape, biconvex, uncoated tablets debossed with the logo of "ZC", "01" and bisect on one side and plain on the other side and are supplied as follows:

NDC: 70518-2488-00

PACKAGING: 30 in 1 BLISTER PACK

Keep tightly closed.

Store at 20°C to 25°C (68°F to 77°F) [See USP Controlled Room Temperature].

Protect from light.

Dispense in light-resistant, tight container.

Repackaged and Distributed By:

Remedy Repack, Inc.

625 Kolter Dr. Suite #4 Indiana, PA 1-724-465-8762

MEDICATION GUIDE

Patient Information Leaflet

Promethazine Hydrochloride Tablets, USP

(proe meth′ a zeen hye″ droe klor′ ide)

This is a summary of the most important information about promethazine. For details, talk to your healthcare professional.

Repackaged By / Distributed By: RemedyRepack Inc.

625 Kolter Drive, Indiana, PA 15701

(724) 465-8762

What Is Promethazine?

Promethazine is an antihistamine which can be taken by mouth as a tablet or syrup, rectally as a suppository, or by injection. It can be used for:

- "hay fever," or, a stuffy runny nose from allergy
- watery, itchy eyes due to inhaled allergies and foods
- mild allergic skin reactions with itching and swelling
- allergic reactions to blood or plasma
- dermographism, a form of hives known as "skin writing"
- serious allergic reactions along with epinephrine and other treatments
- sedation before or after surgery, or during childbirth
- prevention and control of nausea and vomiting after surgery
- along with meperidine (demerol) or other pain medicines
- sedation, relief of anxiety, and production of light sleep
- from which the patient can be easily aroused
- treatment and prevention of motion sickness

Who Should Not Use Promethazine?

Promethazine should not be given to:

- children under two years of age
- patients who are unconscious
- patients who are allergic to promethazine, any of the ingredients in promethazine, or to other phenothiazines
- patients with lung symptoms including asthma
- children who are vomiting unless the vomiting is prolonged and there is a known cause

What Are The Risks?

The following are the major potential risks and side effects of promethazine therapy. However, this list is not complete.

Severe drowsiness and reduced mental alertness.Promethazine may cause drowsiness which may impair your ability to ride a bike, drive a car, or operate machinery. This may be worsened if taken with alcohol or other drugs that also cause central nervous system (CNS) slowing such as sedatives, pain medicines, tranquilizers or certain drugs for depression.

Serious breathing problems.Promethazine should not be used in patients with poor lung function such as chronic obstructive lung disease or breathing problems while sleeping (sleep apnea).

Increased risk of seizures.Promethazine should be used with caution in patients with seizures or who are on other medicines which may also increase the risk of seizures.

Bone-marrow problems and blood cell production.Promethazine should not be used in patients with bone-marrow problems or used with other drugs that affect the bone marrow's production of blood cells.

Neuroleptic malignant syndrome.This potentially deadly syndrome includes symptoms such as fever, muscle rigidity mental changes, changes in pulse or blood pressure, fast heartbeat, increased sweating or irregular heart rhythm.

- The most common side effects aredrowsiness, changes in blood pressure, skin reactions, blood cell changes and breathing problems. Increased excitability or abnormal movements may occur after one dose of promethazine. If they do, consult your doctor about using another medicine.

What Should I Tell My Healthcare Professional?

Before you start taking promethazine,tell your healthcare professional if you:

- have narrow-angle glaucoma
- have an enlarged prostate
- have a stomach ulcer
- have an intestinal blockage
- have a bladder blockage
- have heart problems
- have liver problems
- have breathing or lung problems
- have sleep apnea (breathing problems when sleeping)
- have seizures
- drink alcohol
- are trying to become pregnant, are already pregnant, or are breast-feeding

Can Other Medicines Or Food Affect Promethazine?

Promethazine and certain other medicines can interact with each other. Tell your healthcare professional about all the medicines you take including prescription and non-prescription medicines, vitamins, and herbal supplements. Some medicines may affect how promethazine works or promethazine may affect how your other medicines work. Know the medicines you take. Keep a list of them with you to show your healthcare professional.

Especially tell your healthcare professional if you take:

- medicines that affect your brain such as anti-anxiety medicine, sleeping pills, pain medicines, sedatives, narcotics, antidepressants or tranquilizers
- epinephrine
- a monoamine oxidase inhibitor (MAOI) which is used to treat depression or other mental disorders
- medicines called anticholinergics

Repackaged and Distributed By:

Remedy Repack, Inc.

625 Kolter Dr. Suite #4 Indiana, PA 1-724-465-8762

PACKAGE LABEL

DRUG: Promethazine Hydrochloride

GENERIC: Promethazine Hydrochloride

DOSAGE: TABLET

ADMINSTRATION: ORAL

NDC: 70518-2488-0

COLOR: white

SHAPE: ROUND

SCORE: Two even pieces

SIZE: 6 mm

IMPRINT: ZC;01

PACKAGING: 30 in 1 BLISTER PACK

ACTIVE INGREDIENT(S):

- PROMETHAZINE HYDROCHLORIDE 12.5mg in 1

INACTIVE INGREDIENT(S):

- LACTOSE MONOHYDRATE
- MAGNESIUM STEARATE
- HYDROXYPROPYL CELLULOSE, UNSPECIFIED
- HYDROXYPROPYL CELLULOSE, LOW SUBSTITUTED